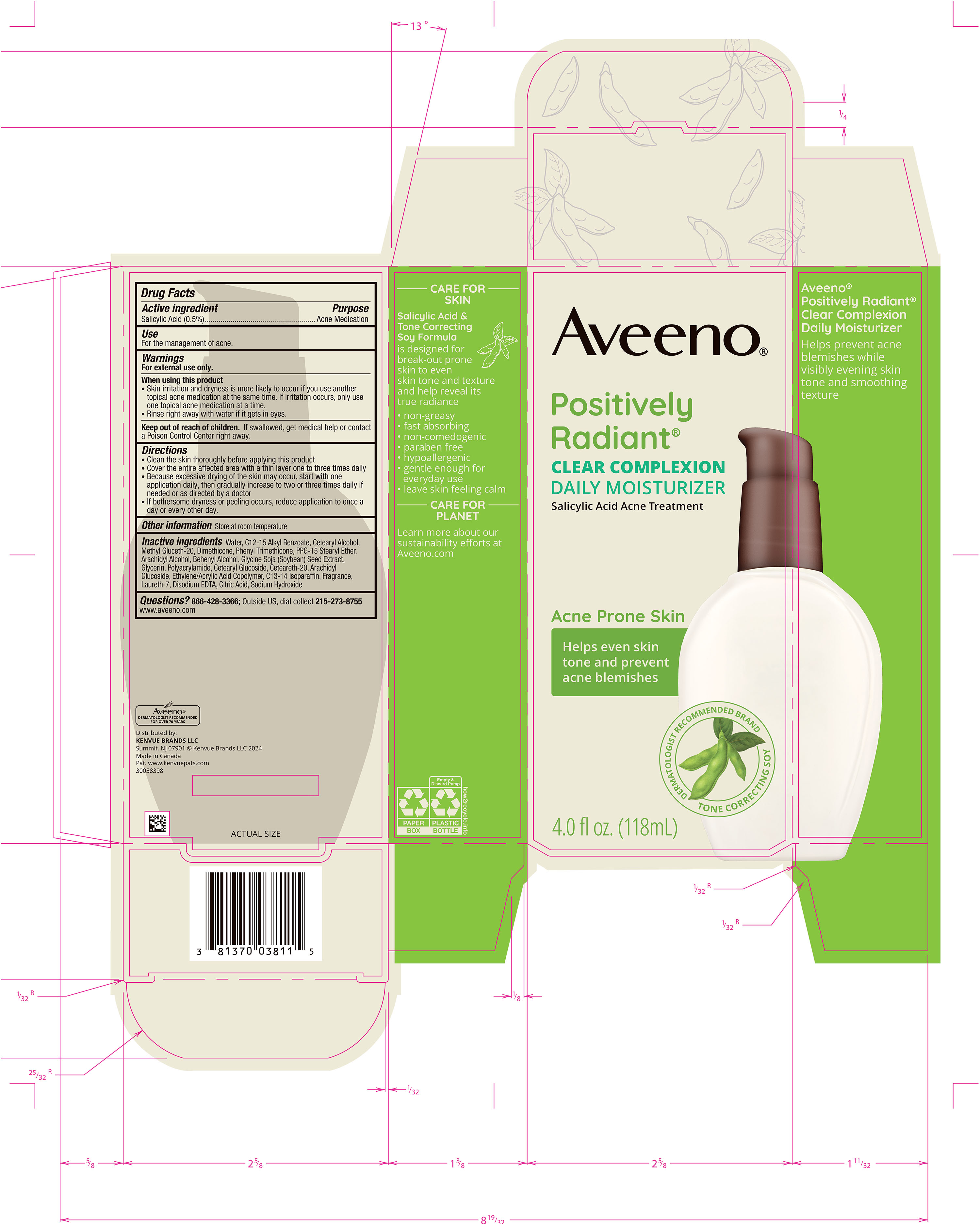 DRUG LABEL: Aveeno Positively Radiant Clear Complexion Daily Moisturizer
NDC: 69968-0928 | Form: LOTION
Manufacturer: Kenvue Brands LLC
Category: otc | Type: HUMAN OTC DRUG LABEL
Date: 20250410

ACTIVE INGREDIENTS: SALICYLIC ACID 5 mg/1 mL
INACTIVE INGREDIENTS: WATER; ALKYL (C12-15) BENZOATE; CETEARYL GLUCOSIDE; POLYOXYL 20 CETOSTEARYL ETHER; LAURETH-7; DIMETHICONE; PHENYL TRIMETHICONE; ARACHIDYL GLUCOSIDE; CETOSTEARYL ALCOHOL; PPG-15 STEARYL ETHER; ARACHIDYL ALCOHOL; DOCOSANOL; GLYCERIN; C13-14 ISOPARAFFIN; EDETATE DISODIUM ANHYDROUS; CITRIC ACID MONOHYDRATE; SOYBEAN; METHYL GLUCETH-20; ACRYLIC ACID/ETHYLENE COPOLYMER (600 MPA.S); SODIUM HYDROXIDE

Aveeno Positively Radiant Clear Complexion Daily Moisturizer

Drug Facts

ACTIVE INGREDIENT

PURPOSE

Salicylic Acid (0.5%)…………………....…………………...Acne Medication

Use

For the management of acne.

Warnings

For external use only.

When using this product

- Skin irritation and dryness is more likely to occur if you use another topical acne medication at the same time. If irritation occurs, only use one topical acne medication at a time.
- Rinse right away with water if it gets in eyes.

Keep out of reach of children. If swallowed, get medical help or contact a Poison Control Center right away.

Directions

- Clean the skin thoroughly before applying this product
- Cover the entire affected area with a thin layer one to three times daily
- Because excessive drying of the skin may occur, start with one application daily, then gradually increase to two or three times daily if needed or as directed by a doctor
- If bothersome dryness or peeling occurs, reduce application to once a day or every other day.

Other information

Store at Room Temperature

Inactive ingredients

Water, C12-15 Alkyl Benzoate, Cetearyl Alcohol, Methyl Gluceth-20, Dimethicone, Phenyl Trimethicone, PPG-15 Stearyl Ether, Arachidyl Alcohol, Behenyl Alcohol, Glycine Soja (Soybean) Seed Extract, Glycerin, Polyacrylamide, Cetearyl Glucoside, Ceteareth-20, Arachidyl Glucoside, Ethylene/Acrylic Acid Copolymer, C13-14 Isoparaffin, Fragrance, Laureth-7, Disodium EDTA, Citric Acid, Sodium Hydroxide

Questions?

866-428-3366; Outside US, dial collect 215-273-8755 www.aveeno.com

Distributed by:
Kenvue Brands LLC
Summit, NJ 07901

PRINCIPAL DISPLAY PANEL - 118 mL Bottle Carton

Aveeno®

Positively

Radiant®

CLEAR COMPLEXION

DAILY MOISTURIZER

Salicylic Acid Acne Treatment

Acne Prone Skin

Helps even skin

tone and prevent

acne blemishes

DERMATOLOGIST RECOMMENDED BRAND

TONE CORRECTING SOY

4.0 fl oz. (118 mL)